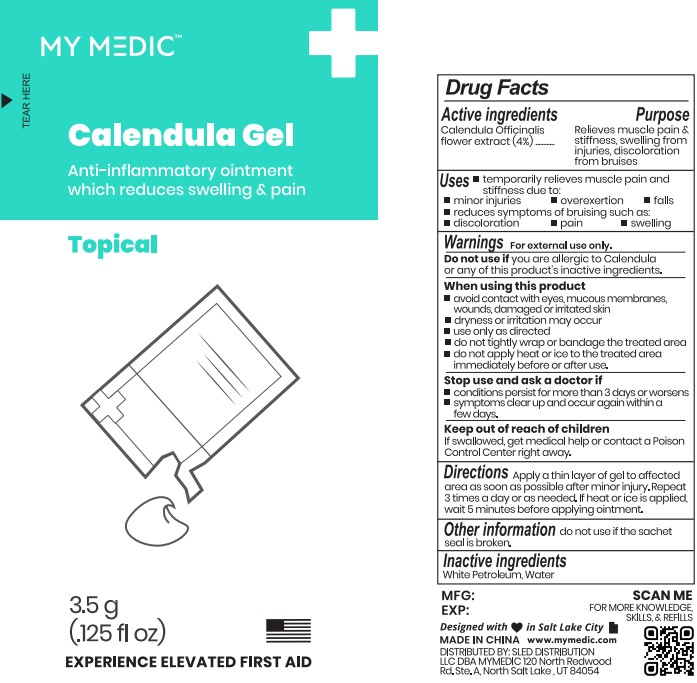 DRUG LABEL: My Medic
NDC: 81417-126 | Form: GEL
Manufacturer: Sled Distribution, LLC
Category: homeopathic | Type: HUMAN OTC DRUG LABEL
Date: 20220407

ACTIVE INGREDIENTS: CALENDULA OFFICINALIS FLOWER 4 g/100 g
INACTIVE INGREDIENTS: WHITE PETROLATUM; WATER

Calendula Gel

Purpose Section

Relieves muscle pain and stiffness, swelling from injuries, discoloration from bruises.

Active Ingredients

Calendula Officinalis Flower Extract ...... 4%

Indications and Usage

temporarily relieve muscle pain and stiffness due to:

- minor infuries
- overexertion
- falls
- reduces symptoms of bruising such as discoloration, pain, and swelling.

Keep our of Reach of Children

if swallowed, get medical help or contact a Poison Control Center right away.

Warning Section

Warnings

For external use only.

■ Do not use on if are allergic to Calendula or any of this product's inactive ingredients.

When using this product

■ avoid contact with eyes, mucous membranes, wounds, damaged or irritated skin.

■dryness or irritation may occur

- Use on as directed
- do not tightly wrap or bandage the treated area
- do not apply heat or ice to the treated area immediately before or after use.

Stop use and ask a doctor if

- conditions persist for more than 3 days or worsens
- symptons clear up and occur again within a few days.

Storange and Handling

Store at room temperature.

Dosage & Administration

apply a thin layer of gel toaffected area as soon as possible after minor injure. Repeat 3 time a day or as needed. If heat or ice is applied, wait 5 minutes before applying ointment.

Inactive Ingredients

White Petroleum, Water